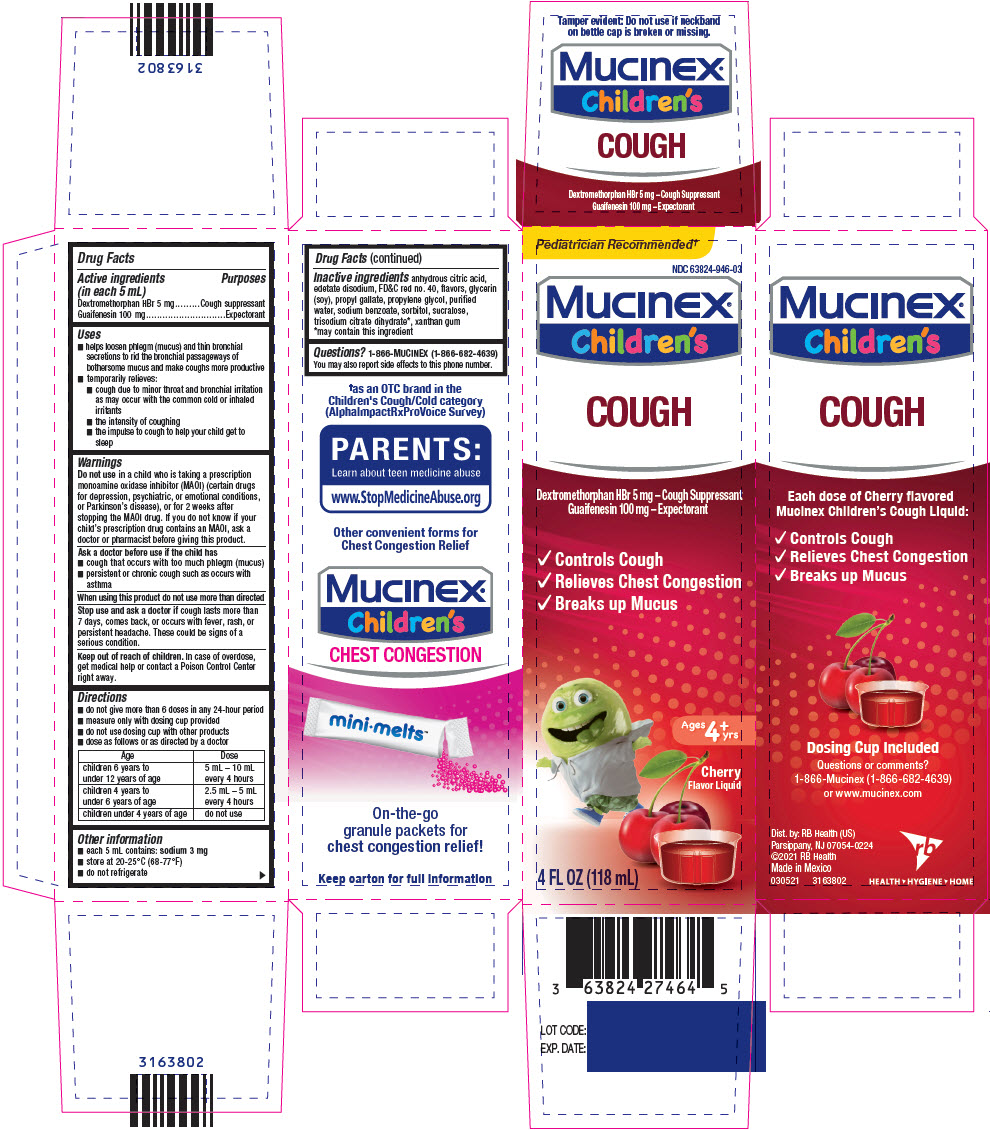 DRUG LABEL: Mucinex Childrens
NDC: 63824-946 | Form: SOLUTION
Manufacturer: RB Health (US) LLC
Category: otc | Type: HUMAN OTC DRUG LABEL
Date: 20250602

ACTIVE INGREDIENTS: DEXTROMETHORPHAN HYDROBROMIDE 5 mg/5 mL; GUAIFENESIN 100 mg/5 mL
INACTIVE INGREDIENTS: ANHYDROUS CITRIC ACID; EDETATE DISODIUM; FD&C RED NO. 40; GLYCERIN; PROPYL GALLATE; PROPYLENE GLYCOL; WATER; SODIUM BENZOATE; SORBITOL; SUCRALOSE; TRISODIUM CITRATE DIHYDRATE; XANTHAN GUM

Mucinex® Children's
Cough

Drug Facts

ACTIVE INGREDIENT

PURPOSE

Active ingredients (in each 5 mL) | Purposes
Dextromethorphan HBr 5 mg | Cough suppressant
Guaifenesin 100 mg | Expectorant

Uses

- helps loosen phlegm (mucus) and thin bronchial secretions to rid the bronchial passageways of bothersome mucus and make coughs more productive
- temporarily relieves:
  - cough due to minor throat and bronchial irritation as may occur with the common cold or inhaled irritants
  - the intensity of coughing
  - the impulse to cough to help your child get to sleep

Warnings

DO NOT USE

Do not usein a child who is taking a prescription monoamine oxidase inhibitor (MAOI) (certain drugs for depression, psychiatric, or emotional conditions, or Parkinson's disease), or for 2 weeks after stopping the MAOI drug. If you do not know if your child's prescription drug contains an MAOI, ask a doctor or pharmacist before giving this product.

Ask a doctor before use if the child has

- cough that occurs with too much phlegm (mucus)
- persistent or chronic cough such as occurs with asthma

When using this product do not use more than directed

Stop use and ask a doctor ifcough lasts more than 7 days, comes back, or occurs with fever, rash, or persistent headache. These could be signs of a serious condition.

Keep out of reach of children.In case of overdose, get medical help or contact a Poison Control Center right away.

Directions

- do not give more than 6 doses in any 24-hour period
- measure only with dosing cup provided
- do not use dosing cup with other products
- dose as follows or as directed by a doctor

Age | Dose
children 6 years to under 12 years of age | 5 mL – 10 mL every 4 hours
children 4 years to under 6 years of age | 2.5 mL – 5 mL every 4 hours
children under 4 years of age | do not use

Other information

- each 5 mL contains: sodium 3 mg
- store between 20-25°C (68-77°F)
- do not refrigerate

Inactive ingredients

anhydrous citric acid, edetate disodium, FD&C red no. 40, flavors, glycerin (soy), propyl gallate, propylene glycol, purified water, sodium benzoate, sorbitol, sucralose, trisodium citrate dihydrate [may contain this ingredient] , xanthan gum

Questions?

1-866-MUCINEX (1-866-682-4639)

You may also report side effects to this phone number.

Dist. by: RB Health (US)
Parsippany, NJ 07054-0224

Made in England

PRINCIPAL DISPLAY PANEL - 118 mL Bottle Carton

Pediatrician Recommended†

NDC 63824-946-03

Mucinex®
Children's

COUGH

Dextromethorphan HBr 5 mg – Cough Suppressant
Guaifenesin 100 mg – Expectorant

- Controls Cough
- Relieves Chest Congestion
- Breaks up Mucus

Ages
4^+yrs

Cherry
Flavor Liquid

4 FL OZ (118 mL)